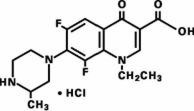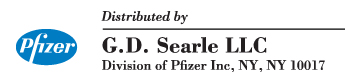 DRUG LABEL: Unknown
Manufacturer: G.D. Searle LLC
Category: prescription | Type: HUMAN PRESCRIPTION DRUG LABELING
Date: 20060511

Maxaquin®
lomefloxacin hydrochloride tablets

To reduce the development of drug-resistant bacteria and maintain the effectiveness of Maxaquin and other antibacterial drugs, Maxaquin should be used only to treat or prevent infections that are proven or strongly suspected to be caused by bacteria.

DESCRIPTION

Maxaquin (lomefloxacin HCl) is a synthetic broad-spectrum antimicrobial agent for oral administration. Lomefloxacin HCl, a difluoroquinolone, is the monohydrochloride salt of (±)-1-ethyl-6,8-difluoro-1,4-dihydro-7-(3-methyl-1-piperazinyl)-4-oxo-3-quinolinecarboxylic acid. Its empirical formula is C17H19F2N3O3•HCl, and its structural formula is:

Lomefloxacin HCl is a white to pale yellow powder with a molecular weight of 387.8. It is slightly soluble in water and practically insoluble in alcohol. Lomefloxacin HCl is stable to heat and moisture but is sensitive to light in dilute aqueous solution.

Maxaquin is available as a film-coated tablet formulation containing 400 mg of lomefloxacin base, present as the hydrochloride salt. The base content of the hydrochloride salt is 90.6%. The inactive ingredients are carboxymethylcellulose calcium, hydroxypropyl cellulose, hypromellose, lactose, magnesium stearate, polyethylene glycol, polyoxyl 40 stearate, and titanium dioxide.

CLINICAL PHARMACOLOGY

Pharmacokinetics in healthy volunteers

In 6 fasting healthy male volunteers, approximately 95% to 98% of a single oral dose of lomefloxacin was absorbed. Absorption was rapid following single doses of 200 and 400 mg (Tmax 0.8 to 1.4 hours). Mean plasma concentration increased proportionally between 100 and 400 mg as shown below:

Dose (mg) | Mean Peak Plasma Concentration (µg/mL) | Area Under Curve (AUC) (µg∙h/mL)
100 | 0.8 | 5.6
200 | 1.4 | 10.9
400 | 3.2 | 26.1

In 6 healthy male volunteers administered 400 mg of lomefloxacin on an empty stomach qd for 7 days, the following mean pharmacokinetic parameter values were obtained:

Cmax | 2.8 µg/mL
Cmin | 0.27 µg/mL
AUC0–24 h | 25.9 µg∙h/mL
Tmax | 1.5 h
t1/2 | 7.75 h

The elimination half-life in 8 subjects with normal renal function was approximately 8 hours. At 24 hours postdose, subjects with normal renal function receiving single doses of 200 or 400 mg had mean plasma lomefloxacin concentrations of 0.10 and 0.24 µg/mL, respectively. Steady-state concentrations were achieved within 48 hours of initiating therapy with one-a-day dosing. There was no drug accumulation with single-daily dosing in patients with normal renal function.

Approximately 65% of an orally administered dose was excreted in the urine as unchanged drug in patients with normal renal function. Following a 400-mg dose of lomefloxacin administered qd for 7 days, the mean urine concentration 4 hours postdose was in excess of 300 µg/mL. The mean urine concentration exceeded 35 µg/mL for at least 24 hours after dosing.

Following a single 400-mg dose, the solubility of lomefloxacin in urine usually exceeded its peak urinary concentration 2- to 6-fold. In this study, urine pH affected the solubility of lomefloxacin with solubilities ranging from 7.8 mg/mL at pH 5.2, to 2.4 mg/mL at pH 6.5, and 3.03 mg/mL at pH 8.12.

The urinary excretion of lomefloxacin was virtually complete within 72 hours after cessation of dosing, with approximately 65% of the dose being recovered as parent drug and 9% as its glucuronide metabolite. The mean renal clearance was 145 mL/min in subjects with normal renal function (GFR = 120 mL/min). This may indicate tubular secretion.

Food effect

When lomefloxacin and food were administered concomitantly, the rate of drug absorption was delayed (Tmax increased to 2 hours [delayed by 41%], Cmax decreased by 18%), and the extent of absorption (AUC) was decreased by 12%.

Pharmacokinetics in the geriatric population

In 16 healthy elderly volunteers (61 to 76 years of age) with normal renal function for their age, the half-life of lomefloxacin (mean of 8 hours) and its peak plasma concentration (mean of 4.2 µg/mL) following a single 400-mg dose were similar to those in 8 younger subjects dosed with a single 400-mg dose. Thus, drug absorption appears unaffected in the elderly. Plasma clearance was, however, reduced in this elderly population by approximately 25%, and the AUC was increased by approximately 33%. This slower elimination most likely reflects the decreased renal function normally observed in the geriatric population.

Pharmacokinetics in renally impaired patients

In 8 patients with creatinine clearance (ClCr) between 10 and 40 mL/min/1.73 m^2, the mean AUC after a single 400-mg dose of lomefloxacin increased 335% over the AUC demonstrated in patients with a ClCr> 80 mL/min/1.73 m^2. Also, in these patients, the mean t1/2 increased to 21 hours. In 8 patients with ClCr< 10 mL/min/1.73 m^2, the mean AUC after a single 400-mg dose of lomefloxacin increased 700% over the AUC demonstrated in patients with a ClCr> 80 mL/min/1.73 m^2. In these patients with ClCr< 10 mL/min/1.73 m^2, the mean t1/2 increased to 45 hours. The plasma clearance of lomefloxacin was closely correlated with creatinine clearance, ranging from 31 mL/min/1.73 m^2 when creatinine clearance was zero to 271 mL/min/1.73 m^2 at a normal creatinine clearance of 110 mL/min/1.73 m^2. Peak lomefloxacin concentrations were not affected by the degree of renal function when single doses of lomefloxacin were administered. Adjustment of dosage schedules for patients with such decreases in renal function is warranted. (See Dosage and Administration.)

Pharmacokinetics in patients with cirrhosis

In 12 patients with histologically confirmed cirrhosis, no significant changes in rate or extent of lomefloxacin exposure (Cmax, Tmax, t1/2, or AUC) were observed when they were administered 400 mg of lomefloxacin as a single dose. No data are available in cirrhotic patients treated with multiple doses of lomefloxacin. Cirrhosis does not appear to reduce the nonrenal clearance of lomefloxacin. There does not appear to be a need for a dosage reduction in cirrhotic patients, provided adequate renal function is present.

Metabolism and pharmacodynamics of lomefloxacin

Lomefloxacin is minimally metabolized although 5 metabolites have been identified in human urine. The glucuronide metabolite is found in the highest concentration and accounts for approximately 9% of the administered dose. The other 4 metabolites together account for < 0.5% of the dose.

Approximately 10% of an oral dose was recovered as unchanged drug in the feces.

Serum protein binding of lomefloxacin is approximately 10%.

The following are mean tissue- or fluid-to-plasma ratios of lomefloxacin following oral administration. Studies have not been conducted to assess the penetration of lomefloxacin into human cerebrospinal fluid.

Tissue or Body Fluid | Mean Tissue- or Fluid-to-Plasma Ratio
Bronchial mucosa | 2.1
Bronchial secretions | 0.6
Prostatic tissue | 2.0
Sputum | 1.3
Urine | 140.0

In two studies including 74 healthy volunteers, the minimal dose of UVA light needed to cause erythema (MED-UVA) was inversely proportional to plasma lomefloxacin concentration. The MED-UVA values (16 hours and 12 hours postdose) were significantly higher than the MED-UVA values 2 hours postdose at steady state. Increasing the interval between lomefloxacin dosing and exposure to UVA light increased the amount of light energy needed for photoreaction. In a study of 27 healthy volunteers, the steady state AUC values and Cmin values were equivalent whether the drug was administered in the morning or in the evening.

Microbiology

Lomefloxacin is a bactericidal agent with in vitro activity against a wide range of gram-negative and gram-positive organisms. The bactericidal action of lomefloxacin results from interference with the activity of the bacterial enzyme DNA gyrase, which is needed for the transcription and replication of bacterial DNA. The minimum bactericidal concentration (MBC) generally does not exceed the minimum inhibitory concentration (MIC) by more than a factor of 2, except for staphylococci, which usually have MBCs 2 to 4 times the MIC.

Lomefloxacin has been shown to be active against most strains of the following organisms both in vitro and in clinical infections: (See Indications and Usage.)

Gram-positive aerobes

Staphylococcus saprophyticus

Gram-negative aerobes

Citrobacter diversus
Enterobacter cloacae
Escherichia coli
Haemophilus influenzae
Klebsiella pneumoniae
Moraxella catarrhalis
Proteus mirabilis
Pseudomonas aeruginosa (urinary tract only—See Indications and Usage and Warnings)

The following in vitro data are available; however, their clinical significance is unknown.

Lomefloxacin exhibits in vitro MICs of 2 µg/mL or less against most strains of the following organisms; however, the safety and effectiveness of lomefloxacin in treating clinical infections due to these organisms have not been established in adequate and well-controlled trials:

Gram-positive aerobes

Staphylococcus aureus (including methicillin-resistant strains)
Staphylococcus epidermidis (including methicillin-resistant strains)

Gram-negative aerobes

Aeromonas hydrophila
Citrobacter freundii
Enterobacter aerogenes
Enterobacter agglomerans
Haemophilus parainfluenzae
Hafnia alvei
Klebsiella oxytoca
Klebsiella ozaenae
Morganella morganii
Proteus vulgaris
Providencia alcalifaciens
Providencia rettgeri
Serratia liquefaciens
Serratia marcescens

Other organisms

Legionella pneumophila

Beta-lactamase production should have no effect on the in vitro activity of lomefloxacin.

Most group A, B, D, and G streptococci, Streptococcus pneumoniae, Pseudomonas cepacia, Ureaplasma urealyticum, Mycoplasma hominis, and anaerobic bacteria are resistant to lomefloxacin.

Lomefloxacin appears slightly less active in vitro when tested at acidic pH. An increase in inoculum size has little effect on the in vitro activity of lomefloxacin. In vitro resistance to lomefloxacin develops slowly (multiple-step mutation). Rapid one-step development of resistance occurs only rarely (< 10^–9) in vitro.

Cross-resistance between lomefloxacin and other quinolone-class antimicrobial agents has been reported; however, cross-resistance between lomefloxacin and members of other classes of antimicrobial agents, such as aminoglycosides, penicillins, tetracyclines, cephalosporins, or sulfonamides has not yet been reported. Lomefloxacin is active in vitro against some strains of cephalosporin- and aminoglycoside-resistant gram-negative bacteria.

Susceptibility tests

Diffusion techniques

Quantitative methods that require measurement of zone diameters give the most precise estimate of the susceptibility of bacteria to antimicrobial agents. One such standardized procedure^1 that has been recommended for use with disks to test the susceptibility of organisms to lomefloxacin uses the 10-µg lomefloxacin disk. Interpretation involves correlation of the diameter obtained in the disk test with the MIC for lomefloxacin.

Reports from the laboratory giving results of the standard single-disk susceptibility test with a 10-µg lomefloxacin disk should be interpreted according to the following criteria:

Zone Diameter (mm) | Interpretation
≥ 22 | Susceptible (S)
19–21 | Intermediate (I)
≤ 18 | Resistant (R)

A report of "susceptible" indicates that the pathogen is likely to be inhibited by generally achievable drug concentrations. A report of "intermediate" indicates that the result should be considered equivocal, and, if the organism is not fully susceptible to alternative clinically feasible drugs, the test should be repeated. This category provides a buffer zone that prevents small uncontrolled technical factors from causing major discrepancies in interpretation. A report of "resistant" indicates that achievable drug concentrations are unlikely to be inhibitory, and other therapy should be selected.

Standardized susceptibility test procedures require the use of laboratory control organisms. The 10-µg lomefloxacin disk should give the following zone diameters:

Organism | Zone Diameter (mm)
S aureus (ATCC 25923) | 23–29
E coli (ATCC 25922) | 27–33
P aeruginosa (ATCC 27853) | 22–28

Dilution techniques

Use a standardized dilution method^2 (broth, agar, or microdilution) or equivalent with lomefloxacin powder. The MIC values obtained should be interpreted according to the following criteria:

MIC (µg/mL) | Interpretation
≤ 2 | Susceptible (S)
4 | Intermediate (I)
≥ 8 | Resistant (R)

As with standard diffusion techniques, dilution methods require the use of laboratory control organisms. Standard lomefloxacin powder should provide the following MIC values:

Organism | MIC (µg/mL)
S aureus (ATCC 29213) | 0.25–2.0
E coli (ATCC 25922) | 0.03–0.12
P aeruginosa (ATCC 27853) | 1.0–4.0

INDICATIONS AND USAGE

Treatment

Maxaquin (lomefloxacin HCl) film-coated tablets are indicated for the treatment of adults with mild to moderate infections caused by susceptible strains of the designated microorganisms in the conditions listed below: (See Dosage and Administration for specific dosing recommendations.)

LOWER RESPIRATORY TRACT

Acute Bacterial Exacerbation of Chronic Bronchitis caused by Haemophilus influenzae or Moraxella catarrhalis. [Although treatment of infections due to this microorganism in this organ system demonstrated a clinically acceptable overall outcome, efficacy was studied in fewer than 10 infections.]

NOTE: MAXAQUIN IS NOT INDICATED FOR THE EMPIRIC TREATMENT OF ACUTE BACTERIAL EXACERBATION OF CHRONIC BRONCHITIS WHEN IT IS PROBABLE THAT S PNEUMONIAE IS A CAUSATIVE PATHOGEN. S PNEUMONIAE EXHIBITS IN VITRO RESISTANCE TO LOMEFLOXACIN, AND THE SAFETY AND EFFICACY OF LOMEFLOXACIN IN THE TREATMENT OF PATIENTS WITH ACUTE BACTERIAL EXACERBATION OF CHRONIC BRONCHITIS CAUSED BY S PNEUMONIAE HAVE NOT BEEN DEMONSTRATED. IF LOMEFLOXACIN IS TO BE PRESCRIBED FOR GRAM–STAIN–GUIDED EMPIRIC THERAPY OF ACUTE BACTERIAL EXACERBATION OF CHRONIC BRONCHITIS, IT SHOULD BE USED ONLY IF SPUTUM GRAM STAIN DEMONSTRATES AN ADEQUATE QUALITY OF SPECIMEN (> 25 PMNs/LPF) AND THERE IS BOTH A PREDOMINANCE OF GRAM-NEGATIVE MICROORGANISMS AND NOT A PREDOMINANCE OF GRAM-POSITIVE MICROORGANISMS.

URINARY TRACT

Uncomplicated Urinary Tract Infections (cystitis) caused by Escherichia coli, Klebsiella pneumoniae, Proteus mirabilis, or Staphylococcus saprophyticus. (See DOSAGE AND ADMINISTRATION and CLINICAL STUDIES—UNCOMPLICATED CYSTITIS.)

Complicated Urinary Tract Infections caused by Escherichia coli, Klebsiella pneumoniae, Proteus mirabilis, Pseudomonas aeruginosa, Citrobacter diversus, or Enterobacter cloacae.

NOTE: In clinical trials with patients experiencing complicated urinary tract infections (UTIs) due to P aeruginosa, 12 of 16 patients had the microorganism eradicated from the urine after therapy with lomefloxacin. None of the patients had concomitant bacteremia. Serum levels of lomefloxacin do not reliably exceed the MIC of Pseudomonas isolates. THE SAFETY AND EFFICACY OF LOMEFLOXACIN IN TREATING PATIENTS WITH PSEUDOMONAS BACTEREMIA HAVE NOT BEEN ESTABLISHED.

Appropriate culture and susceptibility tests should be performed before antimicrobial treatment in order to isolate and identify microorganisms causing infection and to determine their susceptibility to lomefloxacin. In patients with UTIs, therapy with Maxaquin film-coated tablets may be initiated before results of these tests are known; once these results become available, appropriate therapy should be continued. In patients with an acute bacterial exacerbation of chronic bronchitis, therapy should not be started empirically with lomefloxacin when there is a probability the causative pathogen is S pneumoniae.

Beta-lactamase production should have no effect on lomefloxacin activity.

Prevention / prophylaxis

Maxaquin is indicated preoperatively for the prevention of infection in the following situations:

- Transrectal prostate biopsy: to reduce the incidence of urinary tract infection, in the early and late postoperative periods (3–5 days and 3–4 weeks postsurgery).
- Transurethral surgical procedures: to reduce the incidence of urinary tract infection in the early postoperative period (3–5 days postsurgery).

Efficacy in decreasing the incidence of infections other than urinary tract infection has not been established. Maxaquin, like all drugs for prophylaxis of transurethral surgical procedures, usually should not be used in minor urologic procedures for which prophylaxis is not indicated (eg, simple cystoscopy or retrograde pyelography). (See Dosage and Administration.)

To reduce the development of drug-resistant bacteria and maintain the effectiveness of Maxaquin and other antibacterial drugs, Maxaquin should be used only to treat or prevent infections that are proven or strongly suspected to be caused by susceptible bacteria. When culture and susceptibility information are available, they should be considered in selecting or modifying antibacterial therapy. In the absence of such data, local epidemiology and susceptibility patterns may contribute to the empiric selection of therapy.

CONTRAINDICATIONS

Maxaquin (lomefloxacin HCl) is contraindicated in persons with a history of hypersensitivity to lomefloxacin or any member of the quinolone group of antimicrobial agents.

WARNINGS

MODERATE TO SEVERE PHOTOTOXIC REACTIONS HAVE OCCURRED IN PATIENTS EXPOSED TO DIRECT OR INDIRECT SUNLIGHT OR TO ARTIFICIAL ULTRAVIOLET LIGHT (eg, sunlamps) DURING OR FOLLOWING TREATMENT WITH LOMEFLOXACIN. THESE REACTIONS HAVE ALSO OCCURRED IN PATIENTS EXPOSED TO SHADED OR DIFFUSE LIGHT, INCLUDING EXPOSURE THROUGH GLASS. PATIENTS SHOULD BE ADVISED TO DISCONTINUE LOMEFLOXACIN THERAPY AT THE FIRST SIGNS OR SYMPTOMS OF A PHOTOTOXICITY REACTION SUCH AS A SENSATION OF SKIN BURNING, REDNESS, SWELLING, BLISTERS, RASH, ITCHING, OR DERMATITIS.

These phototoxic reactions have occurred with and without the use of sunscreens or sunblocks. Single doses of lomefloxacin have been associated with these types of reactions. In a few cases, recovery was prolonged for several weeks. As with some other types of phototoxicity, there is the potential for exacerbation of the reaction on re-exposure to sunlight or artificial ultraviolet light prior to complete recovery from the reaction. In rare cases, reactions have recurred up to several weeks after stopping lomefloxacin therapy.

EXPOSURE TO DIRECT OR INDIRECT SUNLIGHT (EVEN WHEN USING SUNSCREENS OR SUNBLOCKS) SHOULD BE AVOIDED WHILE TAKING LOMEFLOXACIN AND FOR SEVERAL DAYS FOLLOWING THERAPY. LOMEFLOXACIN THERAPY SHOULD BE DISCONTINUED IMMEDIATELY AT THE FIRST SIGNS OR SYMPTOMS OF PHOTOTOXICITY. RISK OF PHOTOTOXICITY MAY BE REDUCED BY TAKING LOMEFLOXACIN IN THE EVENING (See Dosage and Administration.)

THE SAFETY AND EFFICACY OF LOMEFLOXACIN IN PEDIATRIC PATIENTS AND ADOLESCENTS (UNDER THE AGE OF 18 YEARS), PREGNANT WOMEN, AND LACTATING WOMEN HAVE NOT BEEN ESTABLISHED. (See PRECAUTIONS—Pediatric Use, Pregnancy and Nursing Mothers subsections.) The oral administration of multiple doses of lomefloxacin to juvenile dogs at 0.3 times and to rats at 5.4 times the recommended adult human dose based on mg/m^2 (0.6 and 34 times the recommended adult human dose based on mg/kg, respectively) caused arthropathy and lameness. Histopathologic examination of the weight-bearing joints of these animals revealed permanent lesions of the cartilage. Other quinolones also produce erosions of cartilage of weight-bearing joints and other signs of arthropathy in juvenile animals of various species. (See Animal Pharmacology.)

Convulsions have been reported in patients receiving lomefloxacin. Whether the convulsions were directly related to lomefloxacin administration has not yet been established. However, convulsions, increased intracranial pressure, and toxic psychoses have been reported in patients receiving other quinolones. Nevertheless, lomefloxacin has been associated with a possible increased risk of seizures compared to other quinolones. Some of these may occur with a relative absence of predisposing factors. Quinolones may also cause central nervous system (CNS) stimulation, which may lead to tremors, restlessness, lightheadedness, confusion, and hallucinations. If any of these reactions occurs in patients receiving lomefloxacin, the drug should be discontinued and appropriate measures instituted. However, until more information becomes available, lomefloxacin, like all other quinolones, should be used with caution in patients with known or suspected CNS disorders, such as severe cerebral arteriosclerosis, epilepsy, or other factors that predispose to seizures. (See Adverse Reactions.) Psychiatric disturbances, agitation, anxiety, and sleep disorders may be more common with lomefloxacin than other products in the quinolone class.

The safety and efficacy of lomefloxacin in the treatment of acute bacterial exacerbation of chronic bronchitis due to S pneumoniae have not been demonstrated. This product should not be used empirically in the treatment of acute bacterial exacerbation of chronic bronchitis when it is probable that S pneumoniae is a causative pathogen.

In clinical trials of complicated UTIs due to P aeruginosa, 12 of 16 patients had the microorganism eradicated from the urine after therapy with lomefloxacin. No patients had concomitant bacteremia. Serum levels of lomefloxacin do not reliably exceed the MIC of Pseudomonas isolates. THE SAFETY AND EFFICACY OF LOMEFLOXACIN IN TREATING PATIENTS WITH PSEUDOMONAS BACTEREMIA HAVE NOT BEEN ESTABLISHED.

Serious and occasionally fatal hypersensitivity (anaphylactoid or anaphylactic) reactions, some following the first dose, have been reported in patients receiving quinolone therapy. Some reactions were accompanied by cardiovascular collapse, loss of consciousness, tingling, pharyngeal or facial edema, dyspnea, urticaria, or itching. Only a few of these patients had a history of previous hypersensitivity reactions. Serious hypersensitivity reactions have also been reported following treatment with lomefloxacin. If an allergic reaction to lomefloxacin occurs, discontinue the drug. Serious acute hypersensitivity reactions may require immediate emergency treatment with epinephrine. Oxygen, intravenous fluids, antihistamines, corticosteroids, pressor amines, and airway management, including intubation, should be administered as indicated.

Pseudomembranous colitis has been reported with nearly all antibacterial agents, including lomefloxacin, and may range from mild to life-threatening in severity. Therefore, it is important to consider this diagnosis in patients who present with diarrhea subsequent to the administration of antibacterial agents. Treatment with antimicrobial agents alters the normal flora of the colon and may permit overgrowth of clostridia. Studies indicate that a toxin produced by Clostridium difficile is a primary cause of "antibiotic-associated colitis." After the diagnosis of pseudomembranous colitis has been established, therapeutic measures should be initiated. Mild cases of pseudomembranous colitis usually respond to discontinuation of drug alone. In moderate to severe cases, consideration should be given to management with fluids and electrolytes, protein supplementation, and treatment with an antibacterial drug clinically effective against C difficile colitis.

QT interval prolongation/torsades de pointes

Rare cases of torsades de pointes have been spontaneously reported during post-marketing surveillance in patients receiving quinolones, including lomefloxacin. These rare cases were associated with one or more of the following factors: age over 60, female gender, underlying cardiac disease, and/or use of multiple medications. Lomefloxacin should be avoided in patients with known prolongation of the QT interval, patients with uncorrected hypokalemia, and patients receiving class IA (quinidine, procainamide), or class III (amiodarone, sotalol) antiarrhythmic agents.

Peripheral neuropathy

Rare cases of sensory or sensorimotor axonal polyneuropathy affecting small and/or large axons resulting in paresthesias, hypoesthesias, dysesthesias and weakness have been reported in patients receiving quinolones, including lomefloxacin. Lomefloxacin should be discontinued if the patient experiences symptoms of neuropathy including pain, burning, tingling, numbness, and/or weakness, or is found to have deficits in light touch, pain, temperature, position sense, vibratory sensation, and/or motor strength in order to prevent the development of an irreversible condition.

Tendon effects

Ruptures of the shoulder, hand, Achilles tendon or other tendons that required surgical repair or resulted in prolonged disability have been reported in patients receiving quinolones, including lomefloxacin. Postmarketing surveillance reports indicate that this risk may be increased in patients receiving concomitant corticosteroids, especially the elderly. Lomefloxacin should be discontinued if the patient experiences pain, inflammation, or rupture of a tendon. Patients should rest and refrain from exercise until the diagnosis of tendonitis or tendon rupture has been excluded. Tendon rupture can occur during or after therapy with quinolones, including lomefloxacin.

PRECAUTIONS

General

Alteration of the dosage regimen is recommended for patients with impairment of renal function (ClCr< 40 mL/min/1.73 m^2). (See Dosage and Administration.)

Prescribing Maxaquin in the absence of a proven or strongly suspected bacterial infection or a prophylactic indication is unlikely to provide benefit to the patient and increases the risk of the development of drug-resistant bacteria.

Information for patients

Patients should be advised

- to avoid to the maximum extent possible direct or indirect sunlight (including exposure through glass and exposure through sunscreens and sunblocks) and artificial ultraviolet light (eg sunlamps) during treatment with lomefloxacin and for several days after therapy;
- that they may reduce the risk of developing phototoxicity from sunlight by taking the daily dose of lomefloxacin at least 12 hours before exposure to the sun (eg in the evening);
- to discontinue lomefloxacin therapy at the first signs or symptoms of phototoxicity reaction such as a sensation of skin burning, redness, swelling, blisters, rash, itching, or dermatitis;
- that a patient who has experienced a phototoxic reaction should avoid re-exposure to sunlight and artificial ultraviolet light until he has completely recovered from the reaction. In rare cases, reactions have recurred up to several weeks after stopping lomefloxacin therapy.
- to drink fluids liberally;
- that lomefloxacin can be taken without regard to meals;
- that mineral supplements or vitamins with iron or minerals should not be taken within the 2-hour period before or after taking lomefloxacin (see Drug Interactions);
- that sucralfate and antacids containing magnesium or aluminum, or Videx® (didanosine), chewable/buffered tablets or the pediatric powder for oral solution should not be taken within 4 hours before or 2 hours after taking lomefloxacin. (See PRECAUTIONS — Drug Interactions.)
- that lomefloxacin can cause dizziness and lightheadedness and, therefore, patients should know how they react to lomefloxacin before they operate an automobile or machinery or engage in activities requiring mental alertness and coordination;
- to discontinue treatment and inform their physician if they experience pain, inflammation, or rupture of a tendon, and to rest and refrain from exercise until the diagnosis of tendinitis or tendon rupture has been confidently excluded;
- that lomefloxacin may be associated with hypersensitivity reactions, even following the first dose, and to discontinue the drug at the first sign of a skin rash or other allergic reaction;
- that convulsions have been reported in patients taking quinolones, including lomefloxacin, and to notify their physician before taking this drug if there is a history of this condition.
- that antibacterial drugs including Maxaquin should only be used to treat bacterial infections. They do not treat viral infections (e.g., the common cold). When Maxaquin is prescribed to treat a bacterial infection, patients should be told that although it is common to feel better early in the course of therapy, the medication should be taken exactly as directed. Skipping doses or not completing the full course of therapy may (1) decrease the effectiveness of the immediate treatment and (2) increase the likelihood that bacteria will develop resistance and will not be treatable by Maxaquin or other antibacterial drugs in the future.

Drug interactions

Theophylline

In three pharmacokinetic studies including 46 normal, healthy subjects, theophylline clearance and concentration were not significantly altered by the addition of lomefloxacin. In clinical studies where patients were on chronic theophylline therapy, lomefloxacin had no measurable effect on the mean distribution of theophylline concentrations or the mean estimates of theophylline clearance. Though individual theophylline levels fluctuated, there were no clinically significant symptoms of drug interaction.

Antacids and sucralfate

Sucralfate and antacids containing magnesium or aluminum, as well as formulations containing divalent and trivalent cations such as Videx® (didanosine), chewable/buffered tablets or the pediatric powder for oral solution can form chelation complexes with lomefloxacin and interfere with its bioavailability. Sucralfate administered 2 hours before lomefloxacin resulted in a slower absorption (mean Cmax decreased by 30% and mean Tmax increased by 1 hour) and a lesser extent of absorption (mean AUC decreased by approximately 25%). Magnesium- and aluminum-containing antacids, administered concomitantly with lomefloxacin, significantly decreased the bioavailability (48%) of lomefloxacin. Separating the doses of antacid and lomefloxacin minimizes this decrease in bioavailability; therefore, administration of these agents should precede lomefloxacin dosing by 4 hours or follow lomefloxacin dosing by at least 2 hours.

Caffeine

Two hundred mg of caffeine (equivalent to 1 to 3 cups of American coffee) was administered to 16 normal, healthy volunteers who had achieved steady-state blood concentrations of lomefloxacin after being dosed at 400 mg qd. This did not result in any statistically or clinically relevant changes in the pharmacokinetic parameters of either caffeine or its major metabolite, paraxanthine. No data are available on potential interactions in individuals who consume greater than 200 mg of caffeine per day or in those, such as the geriatric population, who are generally believed to be more susceptible to the development of drug-induced CNS-related adverse effects. Other quinolones have demonstrated moderate to marked interference with the metabolism of caffeine, resulting in a reduced clearance, a prolongation of plasma half-life, and an increase in symptoms that accompany high levels of caffeine.

Cimetidine

Cimetidine has been demonstrated to interfere with the elimination of other quinolones. This interference has resulted in significant increases in half-life and AUC. The interaction between lomefloxacin and cimetidine has not been studied.

Cyclosporine

Elevated serum levels of cyclosporine have been reported with concomitant use of cyclosporine with other members of the quinolone class. Interaction between lomefloxacin and cyclosporine has not been studied.

Omeprazole

No clinically significant changes in lomefloxacin pharmacokinetics (AUC, Cmax, or Tmax) were observed when a single dose of lomefloxacin 400 mg was given after multiple doses of omeprazole (20 mg qd) in 13 healthy volunteers. Changes in omeprazole pharmacokinetics were not studied.

Phenytoin

No significant differences were observed in mean phenytoin AUC, Cmax, Cmin or Tmax (although Cmax increased by 11%) when extended phenytoin sodium capsules (100 mg tid) were coadministered with lomefloxacin (400 mg qd) for five days in 15 healthy males. Lomefloxacin is unlikely to have a significant effect on phenytoin metabolism.

Probenecid

Probenecid slows the renal elimination of lomefloxacin. An increase of 63% in the mean AUC and increases of 50% and 4%, respectively, in the mean Tmax and mean Cmax were noted in 1 study of 6 individuals.

Terfenadine

No clinically significant changes occurred in heart rate or corrected QT intervals, or in terfenadine metabolite or lomefloxacin pharmacokinetics, during concurrent administration of lomefloxacin and terfenadine at steady-state in 28 healthy males.

Warfarin

Quinolones may enhance the effects of the oral anticoagulant, warfarin, or its derivatives. When these products are administered concomitantly, prothrombin or other suitable coagulation tests should be monitored closely. However, no clinically or statistically significant differences in prothrombin time ratio or warfarin enantiomer pharmacokinetics were observed in a small study of 7 healthy males who received both warfarin and lomefloxacin under steady-state conditions.

Carcinogenesis, mutagenesis, impairment of fertility

Carcinogenesis

Hairless (Skh-1) mice were exposed to UVA light for 3.5 hours five times every two weeks for up to 52 weeks while concurrently being administered lomefloxacin. The lomefloxacin doses used in this study caused a phototoxic response. In mice treated with both UVA and lomefloxacin concomitantly, the time to development of skin tumors was 16 weeks. In mice treated concomitantly in this model with both UVA and other quinolones, the times to development of skin tumors ranged from 28 to 52 weeks.

Ninety-two percent (92%) of the mice treated concomitantly with both UVA and lomefloxacin developed well-differentiated squamous cell carcinomas of the skin. These squamous cell carcinomas were nonmetastatic and were endophytic in character. Two-thirds of these squamous cell carcinomas contained large central keratinous inclusion masses and were thought to arise from the vestigial hair follicles in these hairless animals.

In this model, mice treated with lomefloxacin alone did not develop skin or systemic tumors.

There are no data from similar models using pigmented mice and/or fully haired mice

The clinical significance of these findings to humans is unknown.

Mutagenesis

One in vitro mutagenicity test (CHO/HGPRT assay) was weakly positive at lomefloxacin concentrations ≥ 226 µg/mL and negative at concentrations < 226 µg/mL. Two other in vitro mutagenicity tests (chromosomal aberrations in Chinese hamster ovary cells, chromosomal aberrations in human lymphocytes) and two in vivo mouse micronucleus mutagenicity tests were all negative.

Impairment of fertility

Lomefloxacin did not affect the fertility of male and female rats at oral doses up to 8 times the recommended human dose based on mg/m^2 (34 times the recommended human dose based on mg/kg).

Pregnancy

Teratogenic effects. Pregnancy Category C

Reproductive function studies have been performed in rats at doses up to 8 times the recommended human dose based on mg/m^2 (34 times the recommended human dose based on mg/kg), and no impaired fertility or harm to the fetus was reported due to lomefloxacin. Increased incidence of fetal loss in monkeys has been observed at approximately 3 to 6 times the recommended human dose based on mg/m^2 (6 to 12 times the recommended human dose based on mg/kg). No teratogenicity has been observed in rats and monkeys at up to 16 times the recommended human dose exposure. In the rabbit, maternal toxicity and associated fetotoxicity, decreased placental weight, and variations of the coccygeal vertebrae occurred at doses 2 times the recommended human exposure based on mg/m^2. There are, however, no adequate and well-controlled studies in pregnant women. Lomefloxacin should be used during pregnancy only if the potential benefit justifies the potential risk to the fetus.

Nursing mothers

It is not known whether lomefloxacin is excreted in human milk. However, it is known that other drugs of this class are excreted in human milk and that lomefloxacin is excreted in the milk of lactating rats. Because of the potential for serious adverse reactions from lomefloxacin in nursing infants, a decision should be made whether to discontinue nursing or to discontinue the drug, taking into account the importance of the drug to the mother.

Pediatric use

The safety and effectiveness of lomefloxacin in pediatric patients and adolescents less than 18 years of age have not been established. Lomefloxacin causes arthropathy in juvenile animals of several species. (See Warnings and Animal Pharmacology.)

Geriatric use

Of the total number of subjects in clinical studies of lomefloxacin, 25% were ≥ 65 years and 9% were ≥ 75 years. No overall differences in safety or effectiveness were observed between these subjects and younger subjects, and other reported clinical experience has not identified differences in responses between the elderly and younger patients, but greater sensitivity of some older individuals cannot be ruled out.

This drug is known to be substantially excreted by the kidney, and the risk of toxic reactions to this drug may be greater in patients with impaired renal function. Because elderly patients are more likely to have decreased renal function, care should be taken in dose selection, and it may be useful to monitor renal function. (See Clinical Pharmacology — Pharmacokinetics in the geriatric population.)

ADVERSE REACTIONS

In clinical trials, most of the adverse events reported were mild to moderate in severity and transient in nature. During these clinical investigations, 5,623 patients received Maxaquin. In 2.2% of the patients, lomefloxacin was discontinued because of adverse events, primarily involving the gastrointestinal system (0.7%), skin (0.7%), or CNS (0.5%).

Adverse clinical events

The events with the highest incidence (≥ 1%) in patients, regardless of relationship to drug, were headache (3.6%), nausea (3.5%), photosensitivity (2.3%) [see Warnings], dizziness (2.1%), diarrhea (1.4%), and abdominal pain (1.2%).

Additional clinical events reported in < 1% of patients treated with Maxaquin, regardless of relationship to drug, are listed below:

Autonomic: increased sweating, dry mouth, flushing, syncope.

Body as a whole: fatigue, back pain, malaise, asthenia, chest pain, face edema, hot flashes, influenza-like symptoms, edema, chills, allergic reaction, anaphylactoid reaction, decreased heat tolerance.

Cardiovascular: tachycardia, hypertension, hypotension, myocardial infarction, angina pectoris, cardiac failure, bradycardia, arrhythmia, phlebitis, pulmonary embolism, extrasystoles, cerebrovascular disorder, cyanosis, cardiomyopathy.

Central and peripheral nervous system: tremor, vertigo, paresthesias, twitching, hypertonia, convulsions, hyperkinesia, coma.

Gastrointestinal: dyspepsia, vomiting, flatulence, constipation, gastrointestinal bleeding, dysphagia, stomatitis, tongue discoloration, gastrointestinal inflammation.

Hearing: earache, tinnitus.

Hematologic: purpura, lymphadenopathy, thrombocythemia, anemia, thrombocytopenia, increased fibrinolysis.

Hepatic: abnormal liver function.

Metabolic: thirst, hyperglycemia, hypoglycemia, gout.

Musculoskeletal: arthralgia, myalgia, leg cramps.

Ophthalmologic: abnormal vision, conjunctivitis, photophobia, eye pain, abnormal lacrimation.

Psychiatric: insomnia, nervousness, somnolence, anorexia, depression, confusion, agitation, increased appetite, depersonalization, paranoid reaction, anxiety, paroniria, abnormal thinking, concentration impairment.

Reproductive system: Female: vaginal moniliasis, vaginitis, leukorrhea, menstrual disorder, perineal pain, intermenstrual bleeding. Male: epididymitis, orchitis.

Resistance mechanism: viral infection, moniliasis, fungal infection.

Respiratory: respiratory infection, rhinitis, pharyngitis, dyspnea, cough, epistaxis, bronchospasm, respiratory disorder, increased sputum, stridor, respiratory depression.

Skin/Allergic: pruritus, rash, urticaria, skin exfoliation, bullous eruption, eczema, skin disorder, acne, skin discoloration, skin ulceration, angioedema. (See also Body as a whole.)

Special senses: taste perversion.

Urinary: hematuria, micturition disorder, dysuria, strangury, anuria.

Adverse laboratory events

Changes in laboratory parameters, listed as adverse events, without regard to drug relationship include:

Hematologic: monocytosis (0.2%), eosinophilia (0.1%), leukopenia (0.1%), leukocytosis (0.1%).

Renal: elevated BUN (0.1%), decreased potassium (0.1%), increased creatinine (0.1%).

Hepatic: elevations of ALT (SGPT) (0.4%), AST (SGOT) (0.3%), bilirubin (0.1%), alkaline phosphatase (0.1%).

Additional laboratory changes occurring in < 0.1% in the clinical studies included: elevation of serum gamma glutamyl transferase, decrease in total protein or albumin, prolongation of prothrombin time, anemia, decrease in hemoglobin, thrombocythemia, thrombocytopenia, abnormalities of urine specific gravity or serum electrolytes, increased albumin, elevated ESR, albuminuria, macrocytosis.

Post-Marketing Adverse Events

Post-marketing adverse events

Adverse events reported from worldwide marketing experience with lomefloxacin are: anaphylaxis, cardiopulmonary arrest, laryngeal or pulmonary edema, ataxia, cerebral thrombosis, hallucinations, painful oral mucosa, pseudomembranous colitis, hemolytic anemia, hepatitis, tendinitis, diplopia, photophobia, phobia, exfoliative dermatitis, hyperpigmentation, Stevens-Johnson syndrome, toxic epidermal necrolysis, dysgeusia, interstitial nephritis, polyuria, renal failure, urinary retention, and vasculitis.

Quinolone-class adverse events

Additional quinolone-class adverse events include: peripheral neuropathy, torsades de pointes, erythema nodosum, hepatic necrosis, possible exacerbation of myasthenia gravis, dysphasia, nystagmus, intestinal perforation, manic reaction, renal calculi, acidosis and hiccough.

Laboratory adverse events include: agranulocytosis, elevation of serum triglycerides, elevation of serum cholesterol, elevation of blood glucose, elevation of serum potassium, albuminuria, candiduria, and crystalluria.

OVERDOSAGE

Information on overdosage in humans is limited. In the event of acute overdosage, the stomach should be emptied by inducing vomiting or by gastric lavage, and the patient should be carefully observed and given supportive treatment. Adequate hydration must be maintained. Hemodialysis or peritoneal dialysis is unlikely to aid in the removal of lomefloxacin as < 3% is removed by these modalities.

Clinical signs of acute toxicity in rodents progressed from salivation to tremors, decreased activity, dyspnea, and clonic convulsions prior to death. These signs were noted in rats and mice as lomefloxacin doses were increased.

DOSAGE AND ADMINISTRATION

Maxaquin (lomefloxacin HCl) may be taken without regard to meals. Sucralfate and antacids containing magnesium or aluminum, or Videx® (didanosine), chewable/buffered tablets or the pediatric powder for oral solution should not be taken within 4 hours before or 2 hours after taking lomefloxacin. Risk of reaction to solar UVA light may be reduced by taking Maxaquin at least 12 hours before exposure to the sun (eg, in the evening). (See Clinical Pharmacology.)

See Indications and Usage for information on appropriate pathogens and patient populations.

Treatment

Patients with normal renal function

The recommended daily dose of Maxaquin is described in the following chart:

Infection | Unit Dose | Frequency | Duration | Daily Dose
Acute bacterial exacerbation of chronic bronchitis | 400 mg | qd | 10 days | 400 mg
Uncomplicated cystitis in females caused by E coli | 400 mg | qd | 3 days | 400 mg
(see CLINICAL STUDIES—UNCOMPLICATED CYSTITIS.)
Uncomplicated cystitis caused by K pneumoniae, P mirabilis, or S Saprophyticus | 400 mg | qd | 10 days | 400 mg
Complicated UTI | 400 mg | qd | 14 days | 400 mg

Elderly patients

No dosage adjustment is needed for elderly patients with normal renal function (ClCr≥ 40 mL/min/1.73 m^2).

Patients with impaired renal function

Lomefloxacin is primarily eliminated by renal excretion. (See Clinical Pharmacology.) Modification of dosage is recommended in patients with renal dysfunction. In patients with a creatinine clearance > 10 mL/min/1.73 m^2 but < 40 mL/min/1.73 m^2, the recommended dosage is an initial loading dose of 400 mg followed by daily maintenance doses of 200 mg (1/2 tablet) once daily for the duration of treatment. It is suggested that serial determinations of lomefloxacin levels be performed to determine any necessary alteration in the appropriate next dosing interval.

If only the serum creatinine is known, the following formula may be used to estimate creatinine clearance.

Men: (weight in kg) × (140 – age)
(72) × serum creatinine (mg/dL)

Women: (0.85) × (calculated value for men)

Dialysis patients

Hemodialysis removes only a negligible amount of lomefloxacin (3% in 4 hours). Hemodialysis patients should receive an initial loading dose of 400 mg followed by daily maintenance doses of 200 mg (1/2 tablet) once daily for the duration of treatment.

Patients with cirrhosis

Cirrhosis does not reduce the nonrenal clearance of lomefloxacin. The need for a dosage reduction in this population should be based on the degree of renal function of the patient and on the plasma concentrations. (See Clinical Pharmacology and Dosage and Administration—Patients with impaired renal function.)

Prevention / prophylaxis

The recommended dose of Maxaquin is described in the following chart:

Procedure | Dose | Oral Administration
Transrectal prostate biopsy | 400 mg single dose | 1–6 hours prior to procedure
Transurethral surgical procedures [When preoperative prophylaxis is considered appropriate.] | 400 mg single dose | 2–6 hours prior to procedure

HOW SUPPLIED

Maxaquin (lomefloxacin HCl) is supplied as a scored, film-coated tablet containing the equivalent of 400 mg of lomefloxacin base present as the hydrochloride. The tablet is oval, white, and film-coated with "MAXAQUIN 400" debossed on one side and scored on the other side and is supplied in:

NDC Number | Size
0025-5501-01 | bottle of 20

Store at 59° to 77°F (15° to 25°C).

CLINICAL STUDIES—UNCOMPLICATED CYSTITIS

In three controlled clinical studies of uncomplicated cystitis in females, two performed in the United States and one in Canada, lomefloxacin was compared to other oral antimicrobial agents. In these studies, using very strict evaluability criteria and microbiological criteria at 5–9 days posttherapy follow-up, the following bacterial eradication outcomes were obtained:

STUDIES 1, 2, AND 3

U.S. AND CANADIAN STUDIES
 | Lomefloxacin 3-Day Treatment | Norfloxacin 3-Day Treatment | Ofloxacin 3-Day Treatment | Trimethoprim/ sulfamethoxazole 10-Day Treatment
E coli | 133/135 (99%) | 36/39 (92%) | 65/67 (97%) | 33/34 (97%)
K pneumoniae | 7/7 (100%) | 2/2 (100%) | 4/4 (100%) | 2/2 (100%)
P mirabilis | 8/8 (100%) | 1/1 (100%) | 2/2 (100%) | 1/1 (100%)
S saprophyticus | 11/11 (100%) | 3/3 (100%) | 1/1 (100%) | 0/0

STUDY 4

In a controlled clinical study of uncomplicated cystitis performed in Sweden, lomefloxacin 3-day treatment was compared with lomefloxacin 7-day treatment and norfloxacin 7-day treatment. In this study, using very strict evaluability criteria and microbiological criteria at 5–9 days post-therapy follow-up, the following bacterial eradication outcomes were obtained:

SWEDISH STUDY
 | Lomefloxacin 3-Day Treatment | Lomefloxacin 7-Day Treatment | Norfloxacin 7-Day Treatment
E coli | 101/109 (93%) | 102/104 (98%) | 108/110 (98%)
K pneumoniae | 2/2 (100%) | 5/5 (100%) | 1/1 (100%)
P mirabilis | 0/0 | 6/6 (100%) | 4/4 (100%)
S saprophyticus | 11/17 (65%) | 23/23 (100%) | 16/16 (100%)

ANIMAL PHARMACOLOGY

Lomefloxacin and other quinolones have been shown to cause arthropathy in juvenile animals. Arthropathy, involving multiple diarthrodial joints, was observed in juvenile dogs administered lomefloxacin at doses as low as 4.5 mg/kg for 7 to 8 days (0.3 times the recommended human dose based on mg/m^2 or 0.6 times the recommended human dose based on mg/kg). In juvenile rats, no changes were observed in the joints with doses up to 91 mg/kg for 7 days (2 times the recommended human dose based on mg/m^2 or 11 times the recommended human dose based on mg/kg). (See Warnings.)

In a 13-week oral rat study, gamma globulin decreased when lomefloxacin was administered at less than the recommended human exposure. Beta globulin decreased when lomefloxacin was administered at 0.6 to 2 times the recommended human dose based on mg/m^2. The A/G ratio increased when lomefloxacin was administered at 6 to 20 times the human dose. Following a 4-week recovery period, beta globulins in the females and A/G ratios in the females returned to control values. Gamma globulin values in the females and beta and gamma globulins and A/G ratios in the males were still statistically significantly different from control values. No effects on globulins were seen in oral studies in dogs or monkeys in the limited number of specimens collected.

Twenty-seven NSAIDs, administered concomitantly with lomefloxacin, were tested for seizure induction in mice at approximately 2 times the recommended human dose based on mg/m^2. At a dose of lomefloxacin equivalent to the recommended human exposure based on mg/m^2 (10 times the human dose based on mg/kg), only fenbufen, when coadministered, produced an increase in seizures.

Crystalluria and ocular toxicity, seen with some related quinolones, were not observed in any lomefloxacin-treated animals, either in studies designed to look for these effects specifically or in subchronic and chronic toxicity studies in rats, dogs, and monkeys.

Long-term, high-dose systemic use of other quinolones in experimental animals has caused lenticular opacities; however, this finding was not observed with lomefloxacin.

REFERENCES

1. National Committee for Clinical Laboratory Standards, Performance Standards for Antimicrobial Disk Susceptibility Tests—4th ed. Approved Standard NCCLS Document M2–A4, vol 10, No. 7, NCCLS, Villanova, Pa, 1990.
2. National Committee for Clinical Laboratory Standards. Methods for Dilution Antimicrobial Susceptibility Tests for Bacteria that Grow Aerobically—2nd ed. Approved Standard NCCLS Document M7–A2, vol 10, No. 8, NCCLS, Villanova, Pa, 1990.

Rx only

LAB-0141-6.0